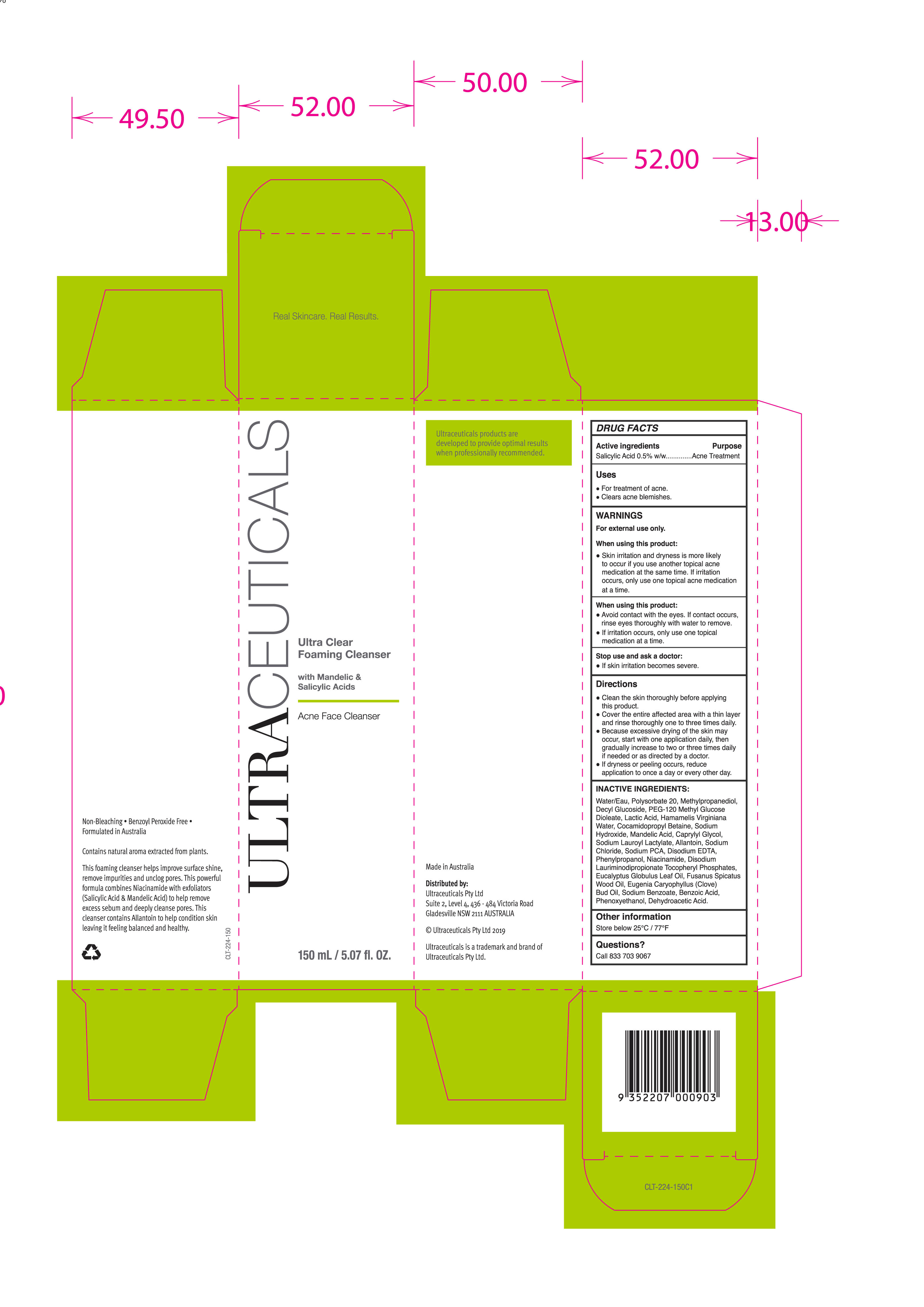 DRUG LABEL: Ultra Clear Foaming Cleanser Acne
NDC: 73122-125 | Form: LOTION
Manufacturer: Ultraceuticals US, LLC
Category: otc | Type: HUMAN OTC DRUG LABEL
Date: 20190925

ACTIVE INGREDIENTS: SALICYLIC ACID 0.5 g/100 mL
INACTIVE INGREDIENTS: METHYLPROPANEDIOL; DECYL GLUCOSIDE; PEG-120 METHYL GLUCOSE DIOLEATE; LACTIC ACID; HAMAMELIS VIRGINIANA TOP WATER; COCAMIDOPROPYL BETAINE; SODIUM HYDROXIDE; POLYSORBATE 20; MANDELIC ACID; CAPRYLYL GLYCOL; DISODIUM LAURIMINODIPROPIONATE TOCOPHERYL PHOSPHATES; SODIUM CHLORIDE; SODIUM PYRROLIDONE CARBOXYLATE; EDETATE DISODIUM; WATER; ALLANTOIN; EUCALYPTUS OIL; SODIUM BENZOATE; DEHYDROACETIC ACID; SANTALUM SPICATUM OIL; PHENYLPROPANOL; NIACINAMIDE; BENZOIC ACID; PHENOXYETHANOL; SODIUM LAUROYL LACTYLATE; CLOVE OIL

Ultra Clear Foaming Cleanser
Acne Face Cleanser

Active Ingredients Purpose

Salicylic Acid 0.5% w/w Acne Treatment

Uses

- For treatment of ACne
- Clear acne blemishes

KEEP OUT OF REACH OF CHILDREN

For external use only

Stop use and ask a doctor:

- if skin irritation becomes severe

Warnings

When using this product:

- Skin irritation and dryness is more likely to occur if you use another topical acne medication at the same time.
- If irritation occurs, only use one topical m

Directions

- Clean the skin thoroughly before applying this product.
- Cover the entire affected area with a thin layer and rinse thoroughly one to three times daily.
- Because excessive drying of the skin may occur, start with one application daily, then gradually increase to two or three times daily if needed or as directed by a doctor
- If dryness or peeling occurs, reduce application to once a day or every other day.

Inactive Ingredient

Water/Eau, Polysorbate 20, Methylpropanediol, Decyl Glucoside, PEG-120 Methyl Glucose Dioleate, Lactic Acid, Hamamelis Virginiana Water, Cocamidopropyl Betain, Sodium Hydroxide, Mandelic Acid, Caprylyl Glycol, Sodium Lauroyl Lactylate, Allantoin, Sodium Chloride, Sodium PCA, Disodium EDTA, Phenylpropanol, Niacinamide, Disodium Lauriminodipropionate Tocopheryl Phosphates, Eucalyptus Globulus Leaf Oil, Fusanus Spicatus Wood Oil, Eugenia Caryophyllus (Clove) Bud Oil, Sodium Benzoate, Benzoic acid, Phenoxyethanol, Dehydroacetic Acid.

PACKAGE LABEL

Ultraceuticals

Ultra Clear Foaming Cleanser

with Mandelic & Salicylic Acid

Acne Face Cleanser